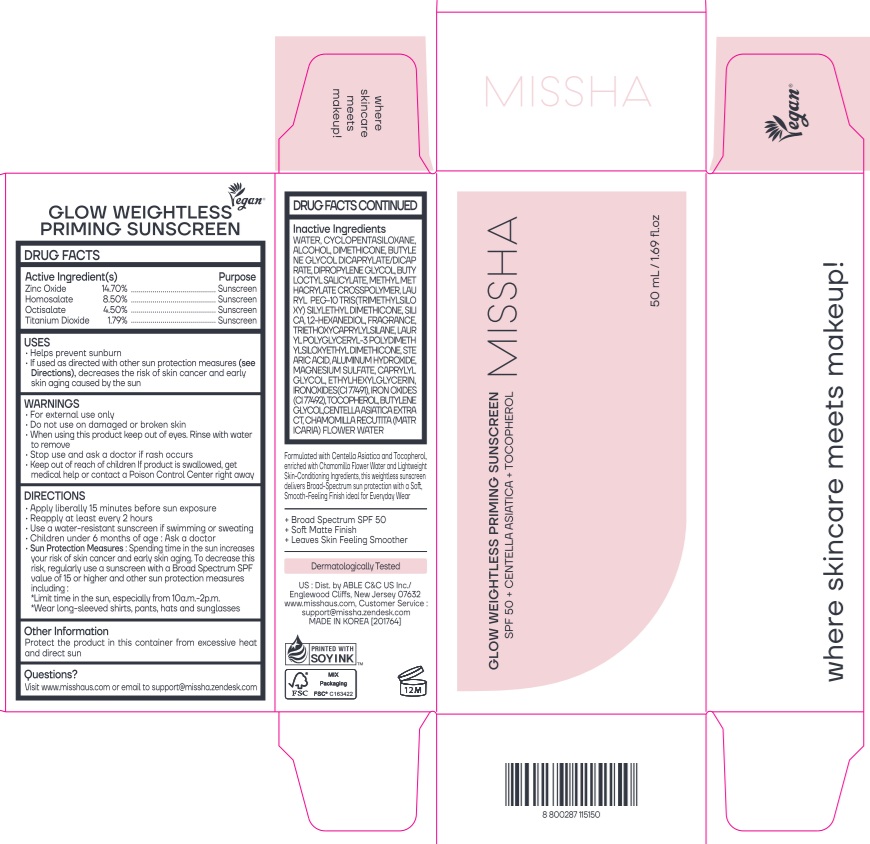 DRUG LABEL: MISSHA GLOW WEIGHTLESS PRIMING SUNSCREEN
NDC: 13733-249 | Form: CREAM
Manufacturer: Able C&C Co., Ltd.
Category: otc | Type: HUMAN OTC DRUG LABEL
Date: 20260122

ACTIVE INGREDIENTS: ZINC OXIDE 14.7 g/100 mL; OCTISALATE 4.5 g/100 mL; HOMOSALATE 8.5 g/100 mL; TITANIUM DIOXIDE 1.79 g/100 mL
INACTIVE INGREDIENTS: DIPROPYLENE GLYCOL; ALCOHOL; DIMETHICONE; BUTYLENE GLYCOL DICAPRYLATE/DICAPRATE; BUTYLOCTYL SALICYLATE; CYCLOMETHICONE 5; WATER

MISSHA GLOW WEIGHTLESS PRIMING SUNSCREEN

Active ingredient(s)
Zinc Oxide 14.70%
Homosalate 8.50%
Octisalate 4.50%
Titanium Dioxide 1.79%

Purpose

Sunscreen

USES

■ Helps prevent sunburn

■ If used as directed with other sun protection measures (See Directions), decreases the risk of skin cancer and early skin aging caused by the sun

WARNINGS

■ For external use only

■ Do not use on damaged or broken skin

■ When using this product keep out of eyes. Rinse with water to remove

■ Stop use and ask a doctor if rash occurs

■ Keep out of reach of children. If product is swallowed, get medical help

or contact a Poison Control Center right away

Keep out of reach of children.

DIRECTIONS

■ Apply liberally 15 minutes before sun exposure

■ Reapply at least every 2 hours

■ Use a water-resistant sunscreen if swimming or sweating

■ Children under 6months of age: Ask a doctor

■ Sun Protection Measures. Spending time in the sun increases your risk of skin cancer and early skin aging. To decrease this risk, regularly use a sunscreen with SPF value of 15 or higher and other sun protection measures including:

* Limit time in the sun, especially from 10a.m.-2p.m.

* Wear long-sleeved shirts, pants, hats and sunglasses

Other Information

Protect the product in this container from excessive heat and direct sun

Questions?

Visit www.misshaus.com or email to support@missha.zendesk.com

Inactive ingredients

WATER, CYCLOPENTASILOXANE, ALCOHOL, DIMETHICONE, BUTYLENE GLYCOL DICAPRYLATE/DICAPRATE, DIPROPYLENE GLYCOL, BUTYLOCTYL SALICYLATE, METHYL METHACRYLATE CROSSPOLYMER, LAURYL PEG-10 TRIS(TRIMETHYLSILOXY)SILYLETHYL DIMETHICONE, SILICA, 1,2-HEXANEDIOL, FRAGRANCE, TRIETHOXYCAPRYLYLSILANE, LAURYL POLYGLYCERYL-3 POLYDIMETHYLSILOXYETHYL DIMETHICONE, STEARIC ACID, ALUMINUM HYDROXIDE, MAGNESIUM SULFATE, CAPRYLYL GLYCOL, ETHYLHEXYLGLYCERIN, IRON OXIDES(CI 77491), IRON OXIDES(CI 77492), TOCOPHEROL, BUTYLENE GLYCOL, CENTELLA ASIATICA EXTRACT, CHAMOMILLA RECUTITA (MATRICARIA) FLOWER WATER